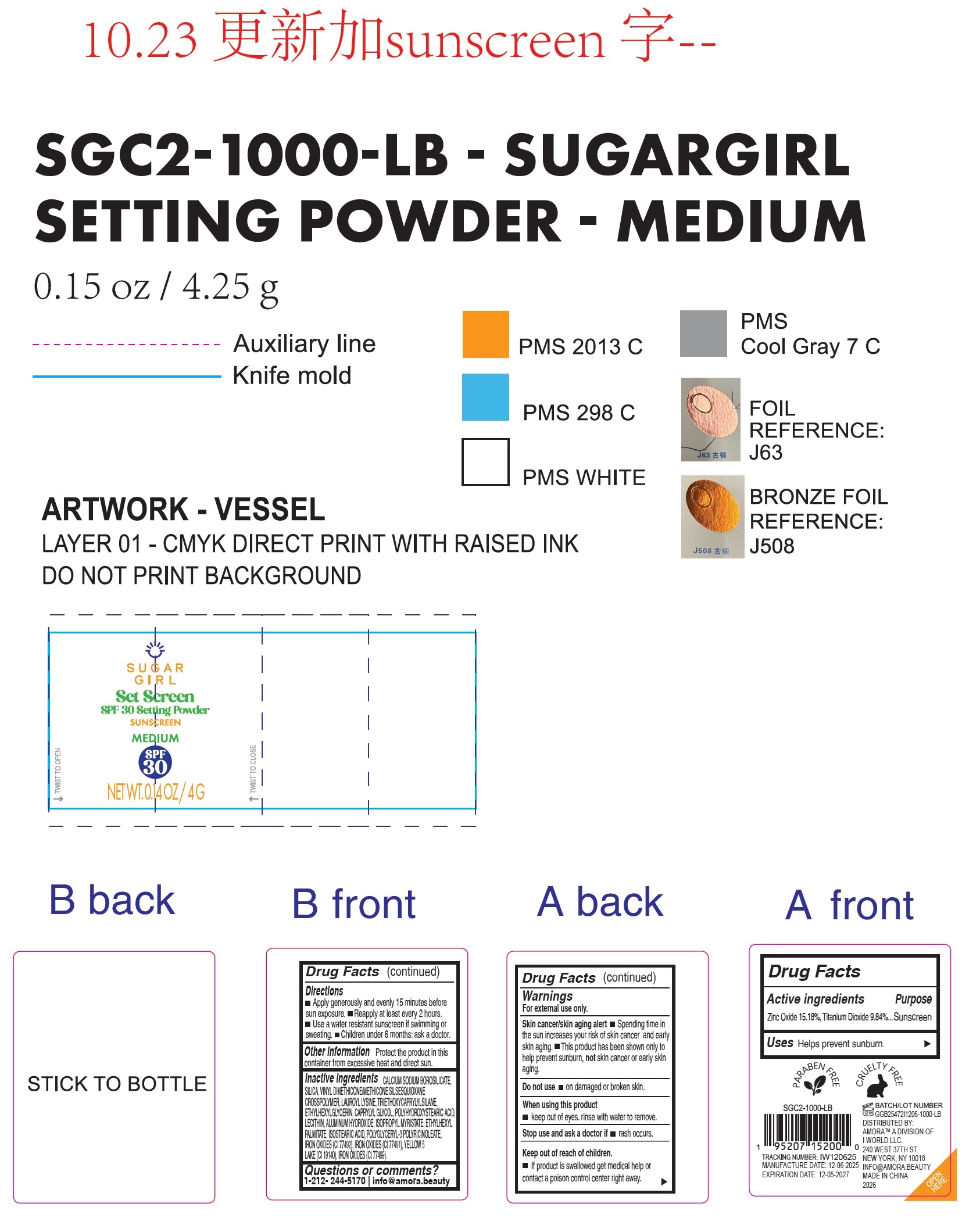 DRUG LABEL: Sugargirl Set Screen SPF 30 Setting Sunscreen Medium
NDC: 85179-034 | Form: POWDER
Manufacturer: I World LLC
Category: otc | Type: HUMAN OTC DRUG LABEL
Date: 20260109

ACTIVE INGREDIENTS: ZINC OXIDE 151.8 mg/1 g; TITANIUM DIOXIDE 98.4 mg/1 g
INACTIVE INGREDIENTS: CALCIUM SODIUM BOROSILICATE; SILICON DIOXIDE; VINYL DIMETHICONE/METHICONE SILSESQUIOXANE CROSSPOLYMER; LAUROYL LYSINE; TRIETHOXYCAPRYLYLSILANE; ETHYLHEXYLGLYCERIN; CAPRYLYL GLYCOL; ALUMINUM HYDROXIDE; ISOPROPYL MYRISTATE; ETHYLHEXYL PALMITATE; ISOSTEARIC ACID; FERRIC OXIDE YELLOW; FERRIC OXIDE RED; FD&C YELLOW NO. 5; FERROSOFERRIC OXIDE

Sugargirl Set Screen SPF 30 Setting Powder Sunscreen Medium

Active ingredients

Zinc Oxide 15.18% Titanium Dioxide 9.84%

Purpose

Sunscreen

Uses

Helps prevent sunburn.

Warnings

For external use only.

Skin cancer/skin aging alert

- Spending time in the sun increases your risk of skin cancer and early skin aging.
- This product has been shown only to help prevent sunburn, not skin cancer or early skin aging.

Do not use

- on damaged or broken skin.
- in the eye area.

When using this product

- keep out of eyes. rinse with water to remove.

Stop use and ask doctor if

- rash occurs.

Keep out of reach of children.

- If product is swallowed get medical help or contact a poison control center right away.

Directions

- Apply generously and evenly 15 minutes before sun exposure.
- Reapply at least every 2 hours.
- Use a water resistant sunscreen if swimming or sweating.
- Children under 6 month: ask a doctor.

Other information

Protect the product in this container from excessive heat and direct sun.

Inactive Ingredients

CALCIUM SODIUM BOROSILICATE, SILICA, VINYL DIMETHICONE/METHICONE SILSESQUIOXANE CROSSPOLYMER, LAUROYL LYSINE, TRIETHOXYCAPRYLYLSILANE, ETHYLHEXYLGLYCERIN, CAPRYLYL GLYCOL, POLYHYDROXYSTEARIC ACID, LECITHIN, ALUMINUM HYDROXIDE, ISOPROPYL MYRISTATE, ETHYLHEXYL PALMITATE, ISOSTEARIC ACID, POLYGLYCERYL-3 POLYRICINOLEATE, IRON OXIDES (CI 77492), IRON OXIDES (CI 77491), YELLOW 5 LAKE (CI 19140), IRON OXIDES (CI 77499).

Questions or comments?

1-212- 244-5170 info@amora.beauty